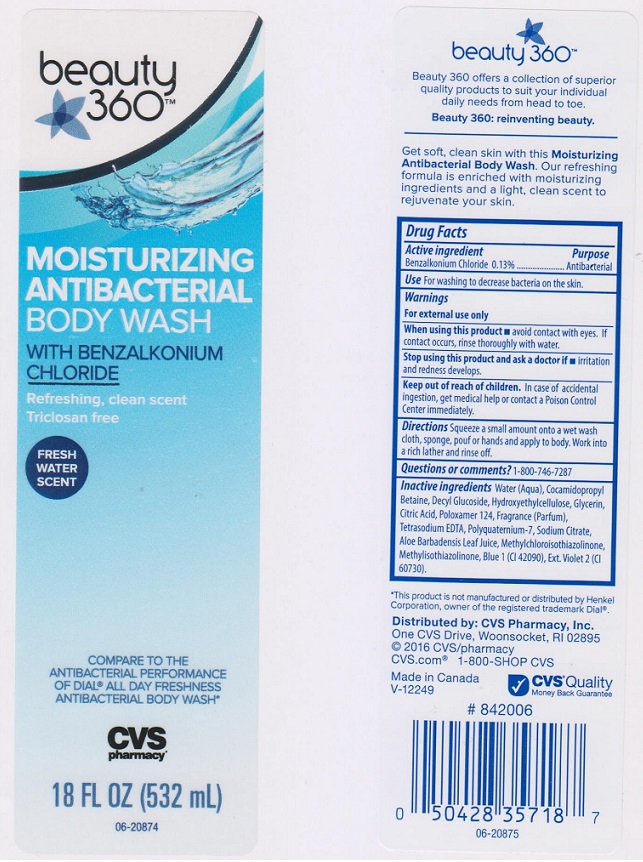 DRUG LABEL: Beauty 360 Antibacterial Moisturizing Body Wash
NDC: 59779-507 | Form: LIQUID
Manufacturer: CVS PHARMACY
Category: otc | Type: HUMAN OTC DRUG LABEL
Date: 20160204

ACTIVE INGREDIENTS: BENZALKONIUM CHLORIDE 1.3 mg/1 mL
INACTIVE INGREDIENTS: WATER; COCAMIDOPROPYL BETAINE; DECYL GLUCOSIDE; HYDROXYETHYL CELLULOSE (5000 CPS AT 1%); GLYCERIN; CITRIC ACID MONOHYDRATE; POLOXAMER 124; EDETATE SODIUM; POLYQUATERNIUM-7 (70/30 ACRYLAMIDE/DADMAC; 1600000 MW); SODIUM CITRATE; ALOE VERA LEAF; METHYLCHLOROISOTHIAZOLINONE; METHYLISOTHIAZOLINONE; FD&C BLUE NO. 1; EXT. D&C VIOLET NO. 2

DRUG FACTS

Active ingredient

Benzalkonium Chloride 0.13%

Purpose

Antibacterial

Use

for washing to decrease bacteria on the skin.

Warnings

For external use only.

When using this product

- avoid contact with eyes. If contact occurs, rinse thoroughly with water.

Stop using this product and ask a doctor if

- irritation and redness develops.

Keep out of reach of children.

In case of accidental ingestion, get medical help or contact a Poison Control Center immediately.

Directions

Squeeze a small amount onto a wet wash cloth, sponge, pouf or hands and apply to body. Work into a rich lather and rinse off.

Questions or comments?

1-800-746-7287

Inactive ingredients

Water (Aqua), Cocamidopropyl Betaine, Decyl Glucoside, Hydroxyethylcellulose, Glycerin, Citric Acid, Poloxamer 124, Fragrance (Parfum), Tetrasodium EDTA, Polyquaternium-7, Sodium Citrate, Aloe Barbadensis Leaf Juice, Methylchloroisothiazolinone, Methylisothiazolinone, Blue 1 (CI 42090), Ext. Violet 2 (CI 60730).